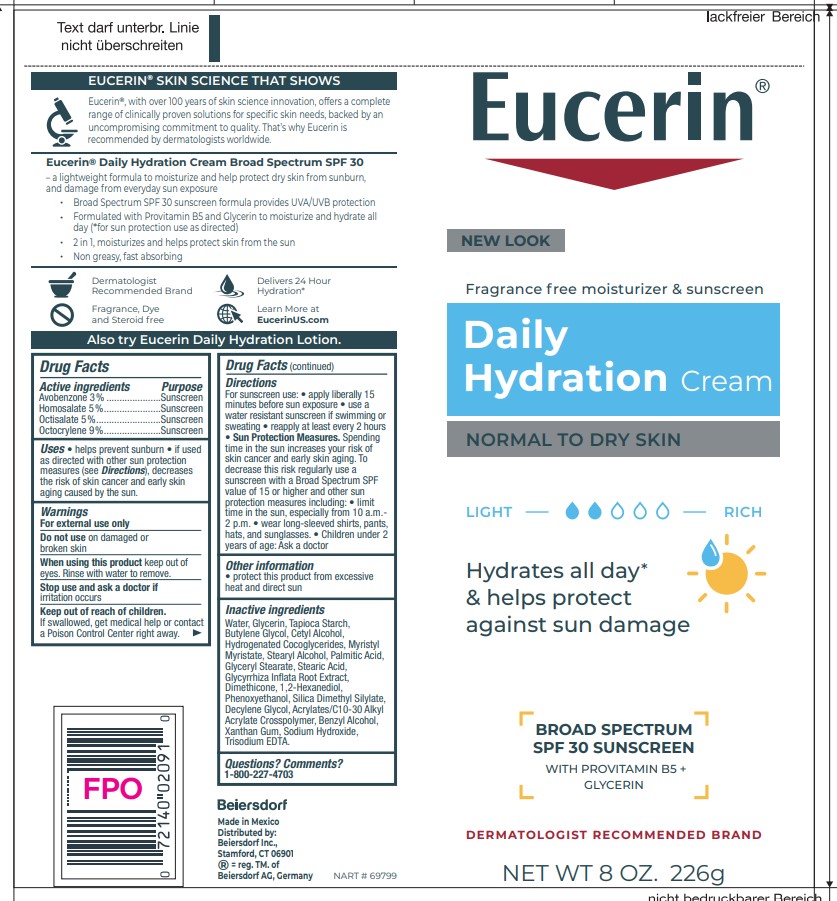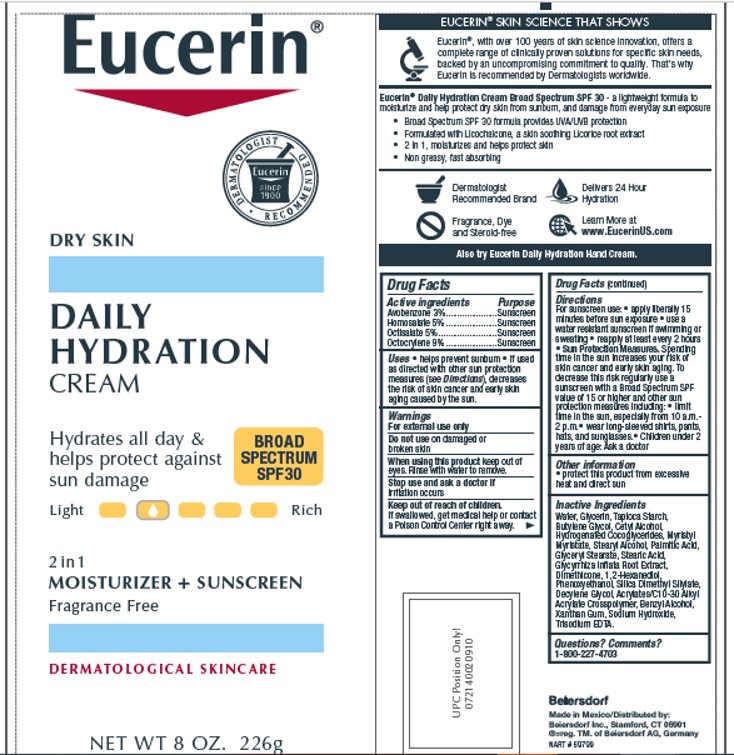 DRUG LABEL: Eucerin Daily Hydration
NDC: 10356-335 | Form: CREAM
Manufacturer: Beiersdorf Inc
Category: otc | Type: HUMAN OTC DRUG LABEL
Date: 20251231

ACTIVE INGREDIENTS: AVOBENZONE 3 g/100 g; HOMOSALATE 5 g/100 g; OCTISALATE 5 g/100 g; OCTOCRYLENE 9 g/100 g
INACTIVE INGREDIENTS: SODIUM HYDROXIDE; EDETATE TRISODIUM; HYDROGENATED COCO-GLYCERIDES; MYRISTYL MYRISTATE; STEARYL ALCOHOL; PALMITIC ACID; GLYCERYL MONOSTEARATE; STEARIC ACID; DIMETHICONE; 1,2-HEXANEDIOL; DECYLENE GLYCOL; XANTHAN GUM; WATER; GLYCERIN; CETYL ALCOHOL; PHENOXYETHANOL; BUTYLENE GLYCOL; BENZYL ALCOHOL; STARCH, TAPIOCA; SILICA DIMETHYL SILYLATE; GLYCYRRHIZA INFLATA ROOT; CARBOMER INTERPOLYMER TYPE A (ALLYL SUCROSE CROSSLINKED)

Eucerin Daily Hydration Cream

Active ingredients
Avobenzone 3%

Homosalate 5%

Octisalate 5%

Octocrylene 9%

Purpose
Sunscreens

Uses
• helps prevent sunburn • if used as directed with other sun protection
measures (see Directions), decreases the risk of skin cancer and early skin aging
caused by the sun.

Warnings
For external use only

Do not use on damaged or broken skin

When using this product keep out of eyes.
Rinse with water to remove

Stop use and ask a doctor if irritation occurs

Keep out of reach of children. If swallowed,
get medical help or contact a Poison Control
Center right away.

Directions
For sunscreen use: • apply liberally 15
minutes before sun exposure • use a water
resistant sunscreen if swimming or sweating
• reapply at least every 2 hours
• Sun Protection Measures. Spending time in
the sun increases your risk of skin cancer and
early skin aging. To decrease this risk regularly
use a sunscreen with a Broad Spectrum SPF
value of 15 or higher and other sun protection
measures including:
• limit time in the sun, especially from
10 a.m.-2 p.m.• wear long-sleeved shirts,
pants, hats, and sunglasses.
• Children under 6 months of age: Ask a doctor

Inactive Ingredients

Water, Glycerin, Tapioca Starch, Butylene Glycol, Cetyl Alcohol,

Hydrogenated Cocoglycerides, Myristyl Myristate, Stearyl Alcohol, Palmitic Acid,

Glyceryl Stearate, Stearic Acid, Glycyrrhiza Inflata Root Extract, Dimethicone,

1,2-Hexanediol, Phenoxyethanol, Silica Dimethyl Silylate, Decylene Glycol,

Acrylates/C10-30 Alkyl Acrylate Crosspolymer, Benzyl Alcohol, Xanthan Gum,

Sodium Hydroxide, Trisodium EDTA.

Questions or comments

1-800-227-4703

PACKAGE LABEL

Eucerin

Daily Hydration
Cream

Dry skin

Hydrates all day and helps protect against sun damage

Broad Spectrum SPF 30

2 in 1 Moisturizer and Sunscreen

Fragrance free

Dermatological skincare

Eucerin

Fragrance free moisturizer and sunscreen

Daily Hydration Cream

Normal to Dry Skin

Hydrates all day and helps protect against sun damage

Broad Spectrum SPF 30 Sunscreen

with Provitamin B5 and Glycerin

Dermatological Recommended Brand